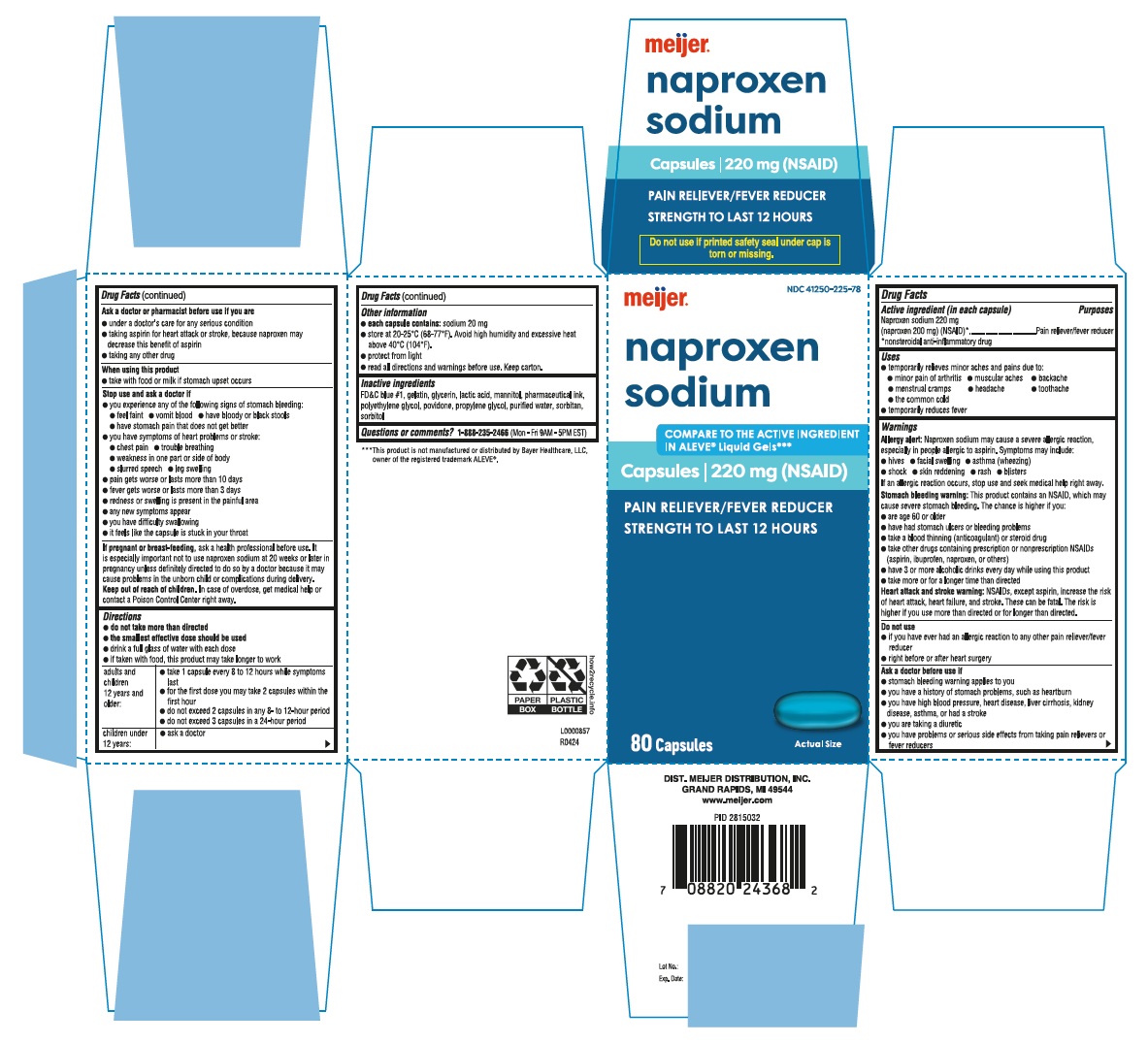 DRUG LABEL: Naproxen Sodium
NDC: 41250-225 | Form: CAPSULE, LIQUID FILLED
Manufacturer: MEIJER DISTRIBUTION INC
Category: otc | Type: HUMAN OTC DRUG LABEL
Date: 20251212

ACTIVE INGREDIENTS: NAPROXEN SODIUM 220 mg/1 1
INACTIVE INGREDIENTS: FD&C BLUE NO. 1; GELATIN; GLYCERIN; LACTIC ACID; MANNITOL; POLYETHYLENE GLYCOL, UNSPECIFIED; POVIDONE; PROPYLENE GLYCOL; WATER; SORBITAN; SORBITOL

Naproxen Sodium Capsules - Meijer

Drug Facts

Active ingredient (in each capsule)

Naproxen sodium 220 mg

(naproxen 200 mg) (NSAID)*

*nonsteroidal anti-inflammatory drug

Purposes

Pain reliever/fever reducer

Uses

- temporarily relieves minor aches and pains due to:
  - minor pain of arthritis
  - muscular aches
  - backache
  - menstrual cramps
  - headache
  - toothache
  - the common cold
- temporarily reduces fever

Warnings

Allergy alert

Naproxen sodium may cause a severe allergic reaction, especially in people allergic to aspirin. Symptoms may include:

- hives
- facial swelling
- asthma (wheezing)
- shock
- skin reddening
- rash
- blisters

If an allergic reaction occurs, stop use and seek medical help right away.

Stomach bleeding warning

This product contains an NSAID, which may cause severe stomach bleeding. The chance is higher if you:

- are age 60 or older
- have had stomach ulcers or bleeding problems
- take a blood thinning (anticoagulant) or steroid drug
- take other drugs containing prescription or nonprescription NSAIDs (aspirin, ibuprofen, naproxen, or others)
- have 3 or more alcoholic drinks every day while using this product
- take more or for a longer time than directed

Heart attack and stroke warning

NSAIDs, except aspirin, increase the risk of heart attack, heart failure, and stroke. These can be fatal. The risk is higher if you use more than directed or for longer than directed.

Do not use

- if you have ever had an allergic reaction to any other pain reliever/fever reducer
- right before or after heart surgery

Ask a doctor before use if

- stomach bleeding warning applies to you
- you have a history of stomach problems, such as heartburn
- you have high blood pressure, heart disease, liver cirrhosis, kidney disease, asthma, or had a stroke
- you are taking a diuretic
- you have problems or serious side effects from taking pain relievers or fever reducers

Ask a doctor or pharmacist before use if you are

- under a doctor's care for any serious condition
- taking aspirin for heart attack or stroke, because naproxen may decrease this benefit of aspirin
- taking any other drug

When using this product

- take with food or milk if stomach upset occurs

Stop use and ask a doctor if

- you experience any of the following signs of stomach bleeding:
- feel faint
- vomit blood
- have bloody or black stools
- have stomach pain that does not get better
- you have symptoms of heart problems or stroke:
- chest pain
- trouble breathing
- weakness in one part or side of body
- slurred speech
- leg swelling
- pain gets worse or lasts more than 10 days
- fever gets worse or lasts more than 3 days
- redness or swelling is present in the painful area
- any new symptoms appear
- you have difficulty swallowing
- it feels like the capsule is stuck in your throat

PREGNANCY OR BREAST FEEDING

If pregnant or breast-feeding,ask a health professional before use. It is especially important not to use naproxen sodium at 20 weeks or later in pregnancy unless definitely directed to do so by a doctor because it may cause problems in the unborn child or complications during delivery.

Keep out of reach of children.In case of overdose, get medical help or contact a Poison Control Center right away.

Directions

- do not take more than directed
- the smallest effective dose should be used
- drink a full glass of water with each dose
- if taken with food, this product may take longer to work

adults and children 12 years and older: | - take 1 capsule every 8 to 12 hours while symptoms last - for the first dose you may take 2 capsules within the first hour - do not exceed 2 capsules in any 8- to 12-hour period - do not exceed 3 capsules in a 24-hour period
children under 12 years: | - ask a doctor

Other information

- each capsule contains:sodium 20 mg
- store at 20-25°C (68-77°F) avoid high humidity and excessive heat above 40°C (104°F)
- protect from light
- read all directions and warnings before use. Keep carton.

Inactive ingredients

FD&C blue #1, gelatin, glycerin, lactic acid, mannitol, pharmaceutical ink, polyethylene glycol, povidone, propylene glycol, purified water, sorbitan, sorbitol

Questions or comments?

1-888-235-2466 (Mon - Fri 9AM - 5PM EST)

***This product is not manufactured or distributed by Bayer Healthcare, LLC, owner of the registered trademark ALEVE®.

Do not use if printed safety seal under cap is torn or missing.

DIST. MEIJER DISTRIBUTION, INC.

GRAND RAPIDS, MI 49544

www.meijer.com

L0000857

R0424

PRINCIPAL DISPLAY PANEL - 220 mg Capsule - 80's Carton

Compare to the active ingredient in ALEVE ® Liquid Gels***

meijer®

naproxen

sodium

Capsules | 220 mg

(NSAID)

Pain Reliever/Fever Reducer

Strength to last 12 hours

80 Capsules

actual size